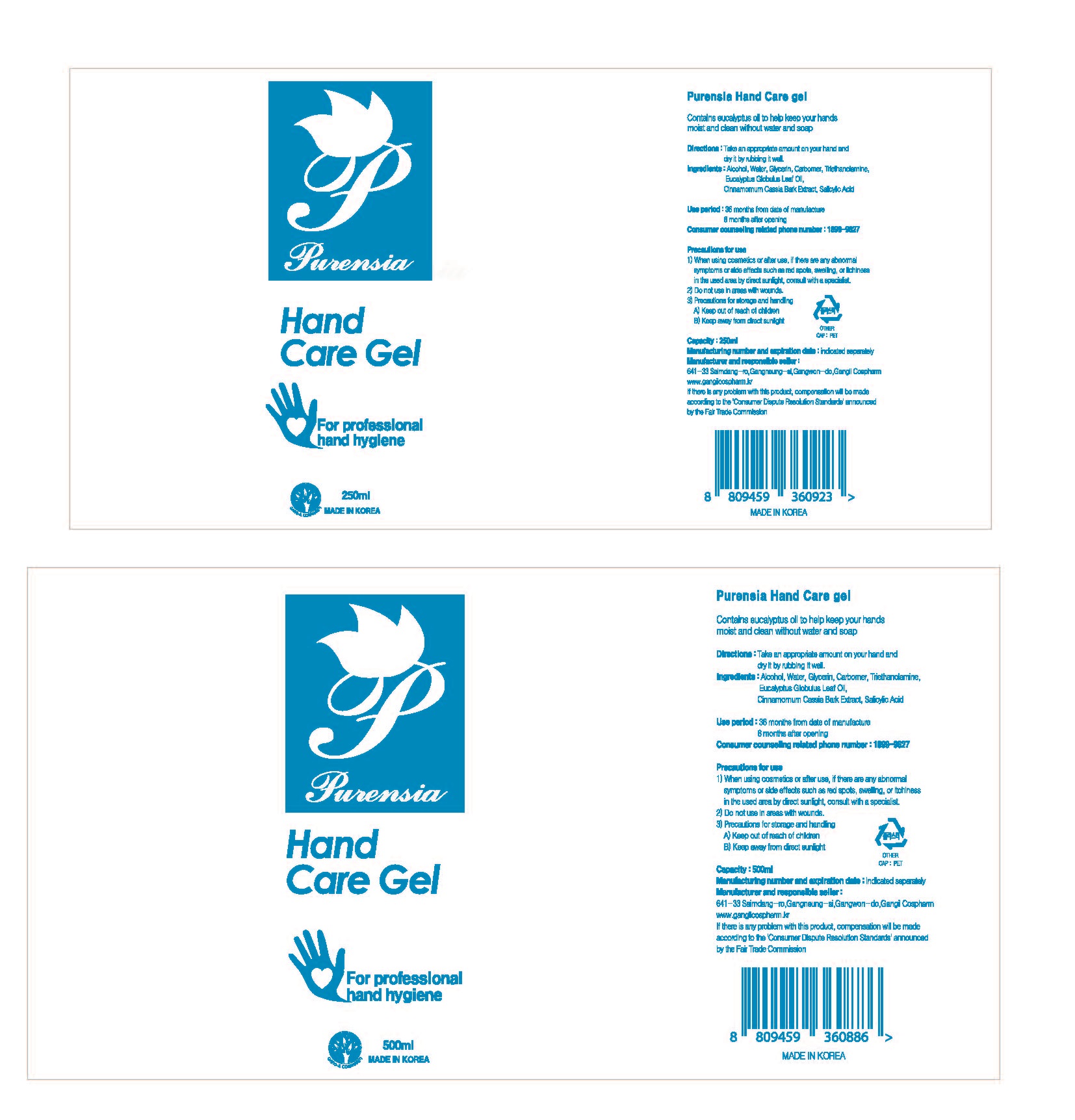 DRUG LABEL: Purensia Hand care gel
NDC: 76646-0001 | Form: GEL
Manufacturer: GANGILCOSPHARM CO LTD
Category: otc | Type: HUMAN OTC DRUG LABEL
Date: 20200424

ACTIVE INGREDIENTS: ALCOHOL 68 mL/100 mL
INACTIVE INGREDIENTS: TROLAMINE; WATER; CARBOMER 940; GLYCERIN

Drug Facts

ACTIVE INGREDIENT

alcohol

PURPOSE

fpr profressional hand hygiene

KEEP OUT OF REACH OF THE CHILDREN

WARNINGS

■ Flammable. Keep away from fire or flame.

■ For external use only.

■ Do not use in eyes.

■ lf swallowed, get medical help promptly.

■ Stop use, ask doctor lf irritation occurs.

■ Keep out of reach of children.

DOSAGE AND ADMINISTRATION

for external use only

INACTIVE INGREDIENT

Water
Glycerin
Carbomer
Triethanolamine
Eucalyptus Globulus Leaf Oil
Cinnamomum Cassia Bark Extract
Salicylic Acid

INDICATIONS AND USAGE

wet hands thoroughly with product and allow to dry without wiping

for children under 6, use only under adult supervision

not recommended for infants